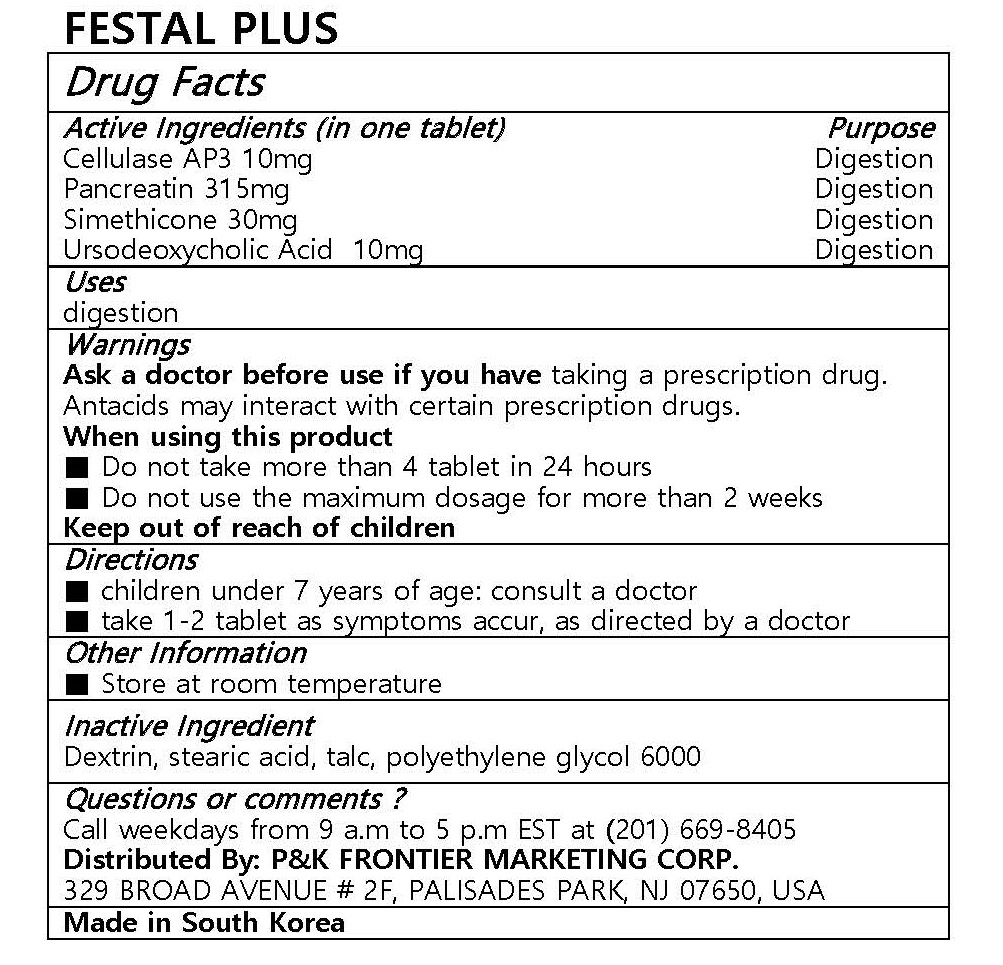 DRUG LABEL: FESTAL PLUS
NDC: 72689-0010 | Form: TABLET
Manufacturer: OASIS TRADING
Category: otc | Type: HUMAN OTC DRUG LABEL
Date: 20181122

ACTIVE INGREDIENTS: URSODIOL 10 mg/1 1; PANCRELIPASE 315 mg/1 1; DIMETHICONE 30 mg/1 1
INACTIVE INGREDIENTS: STEARIC ACID; TALC; POLYETHYLENE GLYCOL 6000

ACTIVE INGREDIENT

Ursodeoxycholic Acid, Pancreatin, Simethione

PURPOSE

digestion

Keep out of reach of children

INDICATIONS AND USAGE

children under 7 years of age: consult a doctor
take 1-2 tablet as symptoms accur, as directed by a doctor

Ask a doctor before use if you have taking a prescription drug. Antacids may interact with certain prescription drugs.
When using this product
■ Do not take more than 4 tablet in 24 hours
■ Do not use the maximum dosage for more than 2 weeks
Keep out of reach of children

INACTIVE INGREDIENT

Dextrin, stearic acid, talc, polyethylene glycol 6000, Cellulase AP3

DOSAGE AND ADMINISTRATION

For oral use only